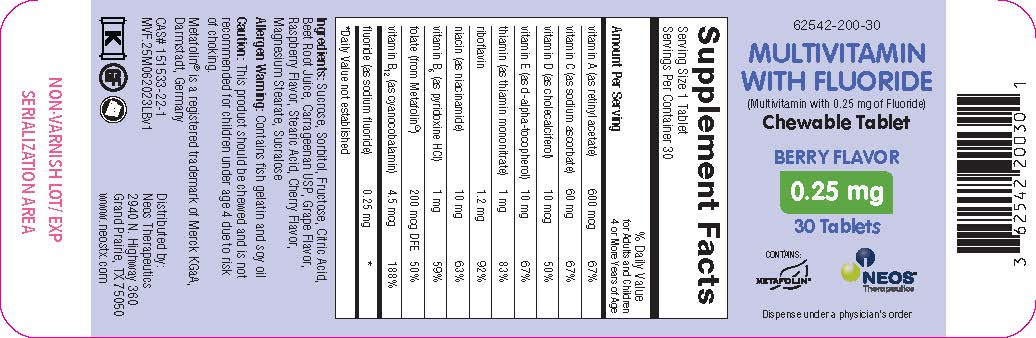 DRUG LABEL: Multivitamin with 0.25 mg Fluoride
NDC: 62542-200 | Form: TABLET, CHEWABLE
Manufacturer: Neos Therapeutics, LP
Category: other | Type: DIETARY SUPPLEMENT
Date: 20230706

ACTIVE INGREDIENTS: VITAMIN A ACETATE 600 ug/1 1; SODIUM ASCORBATE 60 mg/1 1; CHOLECALCIFEROL 10 ug/1 1; .ALPHA.-TOCOPHEROL, D- 10 mg/1 1; THIAMINE MONONITRATE 1 mg/1 1; RIBOFLAVIN 1.2 mg/1 1; NIACINAMIDE 10 mg/1 1; PYRIDOXINE HYDROCHLORIDE 1 mg/1 1; CYANOCOBALAMIN 4.5 ug/1 1; SODIUM FLUORIDE 0.25 mg/1 1
INACTIVE INGREDIENTS: SUCROSE; SORBITOL; FRUCTOSE; CITRIC ACID MONOHYDRATE; CARRAGEENAN; STEARIC ACID; MAGNESIUM STEARATE; SUCRALOSE

Multivitamin-025-tablets

Multivitamin with Fluoride

(Multivitamin with 0.25 mg of Fluoride) Chewable Tablet

Health Claim

Supplement Facts
Serving Size 1 Tablet
Servings Per Container 30
Amount Per Serving | % Daily Value for Adults and Children 4 or More Years of Age
Vitamin A (as retinyl acetate) | 600 mcg | 67%
Vitamin C (as sodium ascorbate) | 60 mg | 67%
Vitamin D (as cholecalciferol) | 10 mcg | 50%
Vitamin E (as d-alpha-tocopherol) | 10 mg | 67%
Thiamin (as thiamin mononitrate | 1 mg | 83%
Riboflavin | 1.2 mg | 92%
Niacin (as niacinamide) | 10 mg | 63%
Vitamin B6 (as pyridoxine HCl) | 1 mg | 59%
Folate (as Metafolin®) | 200 mcg DFE | 50%
Vitamin B12 (as cyanocobalamin) | 4.5 mcg | 188%
Fluoride (as sodium fluoride) | 0.25 mg | *
*Daily Value not established

Ingredients: Sucrose, Sorbitol, Fructose, Citric Acid, Beet Root Juice, Carrageenan USP, Grape Flavor, Raspberry Flavor, Stearic Acid, Cherry Flavor, Magnesium Stearate, Sucralose.

Warnings

Allergen Warning: Contains fish gelatin and soy oil.

Dosage and Administration

Caution: This product should be chewed and is not recommended for children under age 4 due to risk of choking.

Safe Handling Warning

Metafolin® is a registered trademark of Merck KGaA, Darmstadt, Germany

Distributed by:
Neos Therapeutics
2940 N. Highway 360
Grand Prairie, TX 75050
www.neostx.com

Principal Display Panel

62542-200-30

Multivitamin with Fluoride

(Multivitamin with 0.25 mg of Fluoride) Chewable Tablet

BERRY FLAVOR

0.25 mg

30 Tablets

CONTAINS:METAFOLIN®

NEOS THERAPEUTICS